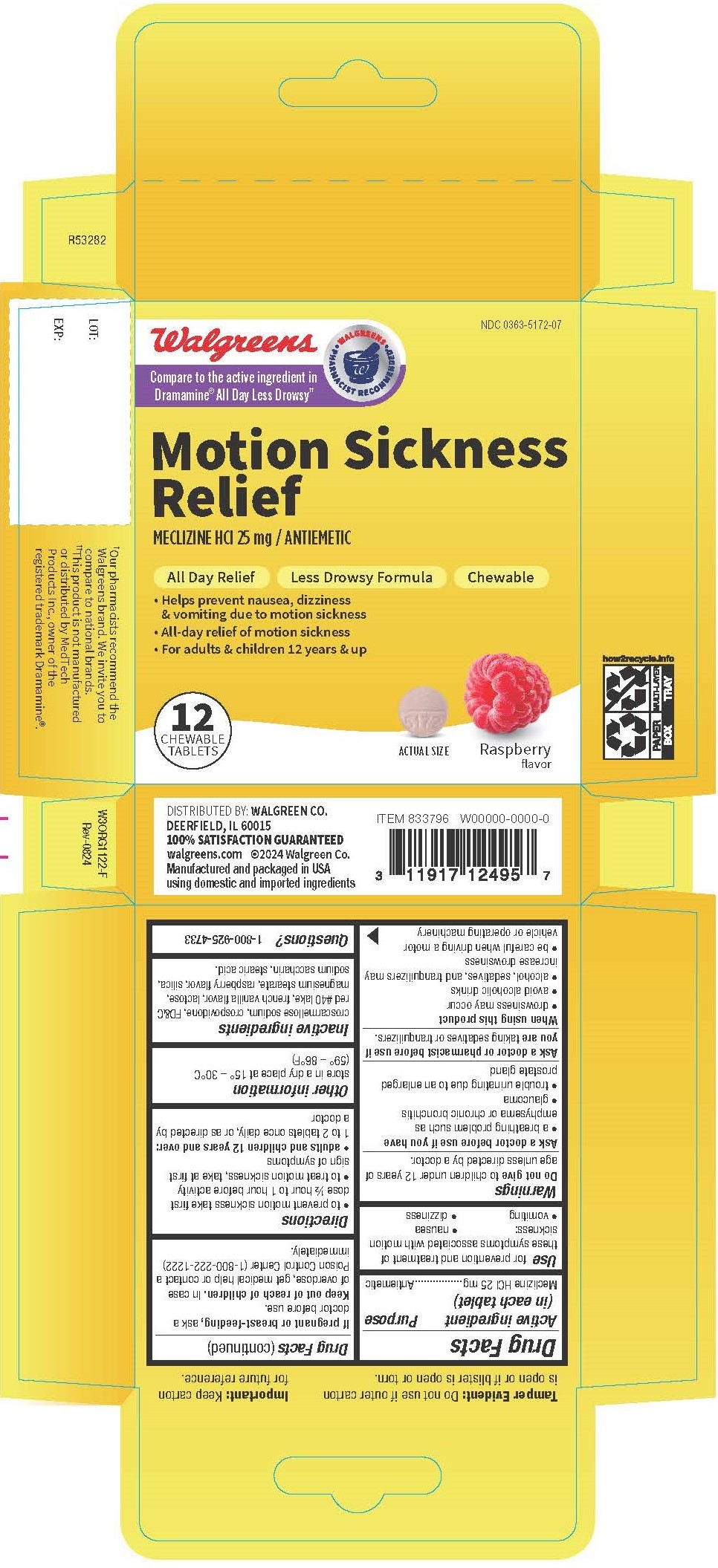 DRUG LABEL: Meclizine Hydrochloride
NDC: 0363-5172 | Form: TABLET, CHEWABLE
Manufacturer: Walgreen Company
Category: otc | Type: HUMAN OTC DRUG LABEL
Date: 20250311

ACTIVE INGREDIENTS: MECLIZINE HYDROCHLORIDE 25 mg/1 1
INACTIVE INGREDIENTS: SILICON DIOXIDE; STEARIC ACID; VANILLA; LACTOSE MONOHYDRATE; MAGNESIUM STEARATE; RASPBERRY; CROSCARMELLOSE SODIUM; CROSPOVIDONE; SACCHARIN SODIUM; FD&C RED NO. 40

5172C-Walgreen

Drug Facts

Active ingredient (in each tablet)
Meclizine HCl 25 mg

Purpose
Antiemetic

Uses

for prevention and treatment of these symptoms associated with motion sickness:

- nausea
- vomiting
- dizziness

WARNINGS

Do not give to children under 12 years of age unless directed by a doctor.

Ask a doctor before use if you have

- a breathing problem such as emphysema or chronic bronchitis
- glaucoma
- trouble urinating due to an enlarged prostate gland

Ask a doctor or pharmacist before use if you are taking sedatives or tranquilizers.

When using this product

- drowsiness may occur
- avoid alcoholic drinks
- alcohol, sedatives, and tranquilizers may increase drowsiness
- be careful when driving a motor vehicle or operating machinery

PREGNANCY OR BREAST FEEDING

If pregnant or breast-feeding, ask a doctor before use.

Keep out of reach of children.

OVERDOSAGE

In case of overdose, get medical help or contact a Poison Control Center (1-800-222-1222) immediately.

Directions

• to prevent motion sickness take first dose ½ hour to 1 hour before activity
• to treat motion sickness, take at first sign of symptoms
• adults and children 12 years and over: 1 to 2 tablets once daily, or as directed by a doctor

Other information

store in a dry place at 15° – 30°C (59° – 86°F)

INACTIVE INGREDIENT

croscarmellose sodium, crospovidone, FD&C red #40 lake, french vanilla flavor, lactose, magnesium stearate, raspberry flavor, silica, sodium saccharin, stearic acid.

QUESTIONS

1-800-925-4733

Tamper Evident: Do not use if outer carton is open or if blister is open or torn.

Important: Keep carton for future reference.

†Our pharmacists recommend the Walgreens brand. We invite you to compare to national brands.
††This product is not manufactured or distributed by MedTech Products Inc., owner of the registered trademark Dramamine®.

DISTRIBUTED BY: WALGREEN CO.
DEERFIELD, IL 60015
100% SATISFACTION GUARANTEED
walgreens.com ©2024 Walgreen Co.
Manufactured and packaged in USA using domestic and imported ingredients

PACKAGE LABEL

NDC 0363-5172-07

Compare to the active ingredient in Dramamine® All Day Less Drowsy††

Motion Sickness Relief

MECLIZINE HCl 25 mg / ANTIEMETIC

All Day Relief

Less Drowsy Formula

Chewable

Helps prevent nausea, dizziness & vomiting due to motion sickness

All-day relief of motion sickness

For adults & children 12 years & up

Raspberry flavor

12 Chewable Tablets